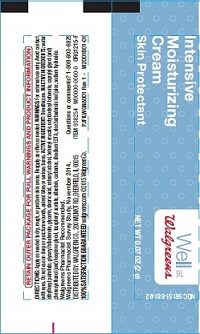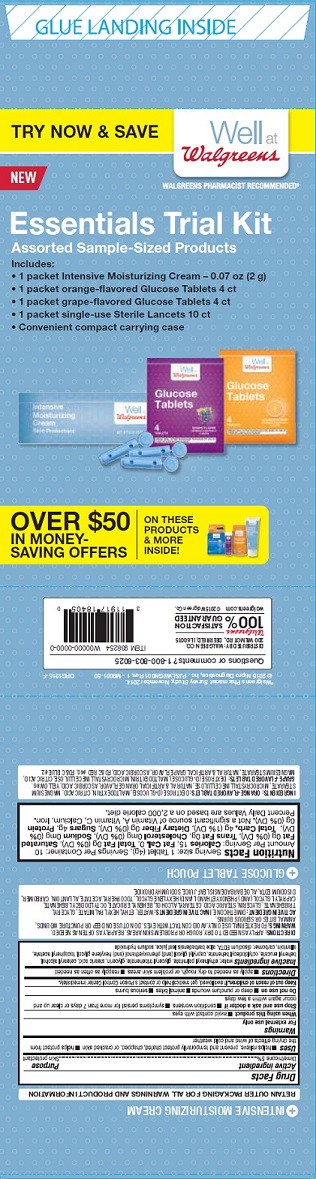 DRUG LABEL: Essentials Trial Kit
NDC: 56151-683 | Form: KIT | Route: TOPICAL
Manufacturer: Trividia Health, Inc.
Category: otc | Type: HUMAN OTC DRUG LABEL
Date: 20191219

ACTIVE INGREDIENTS: DIMETHICONE 5 g/100 g
INACTIVE INGREDIENTS: SODIUM HYDROXIDE; ALPHA-TOCOPHEROL ACETATE; ALOE; ETHYLHEXYL PALMITATE; STEARIC ACID; CAPRYLYL GLYCOL; GLYCERIN; EDETATE DISODIUM; ALLANTOIN; TRIBEHENIN; CARBOMER INTERPOLYMER TYPE A (55000 CPS); HEXYLENE GLYCOL; CETOSTEARYL ALCOHOL; WATER; PHENOXYETHANOL; OCTYLDODECYL BEHENATE; BEHENYL ERUCATE

Essentials Trial Kit

Active Ingredient

Dimethicone 5%

Purpose

Skin protectant

Uses

Helps relieve, prevent and temporarily protect chafed, chapped or cracked skin. helps protect from the drying effects of wind and cold weather

Warnings

For external use only

When using this product

avoid contact with eyes

Stop use and ask a doctor if

condition worsens, symptoms persist for more than 7 days or clear up and occur again within a few days

Do not use on

deep or puncture wounds, animal bites, serious burns

Keep out of reach of children

If swallowed, get medical help or contact a Poison Control Center immediately

Directions

apply as needed to dry, rough, or problem skin areas, reapply as often as needed

Inactive Ingredients

water, ethylhexyl palmitate, glyceryl tribehenate, glycerin, stearic acid, cetearyl alcohol, behenyl erucate, octyldodecyl behenate, caprylyl glycol (and) phenoxyethanol (and) hexylene glycol, tocopheryl acetate, allantoin, carbomer, disodium EDTA, aloe barbadensis leaf juice, sodium hydroxide